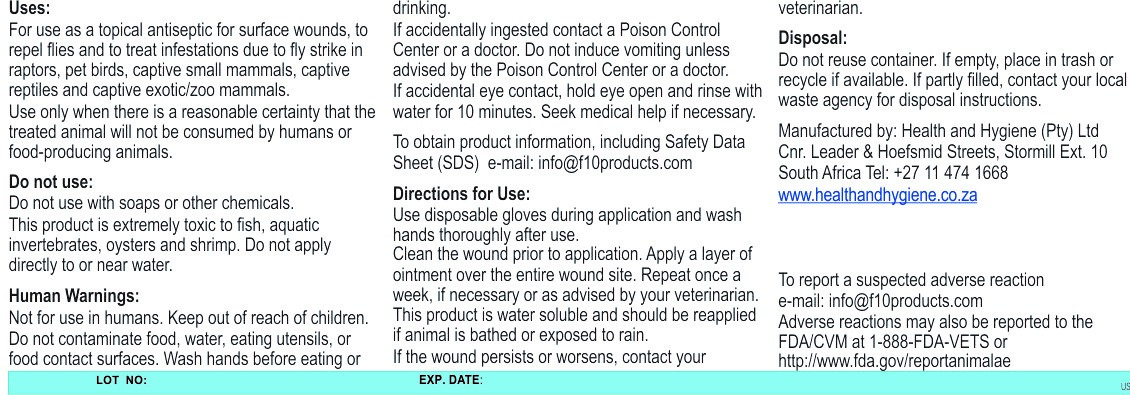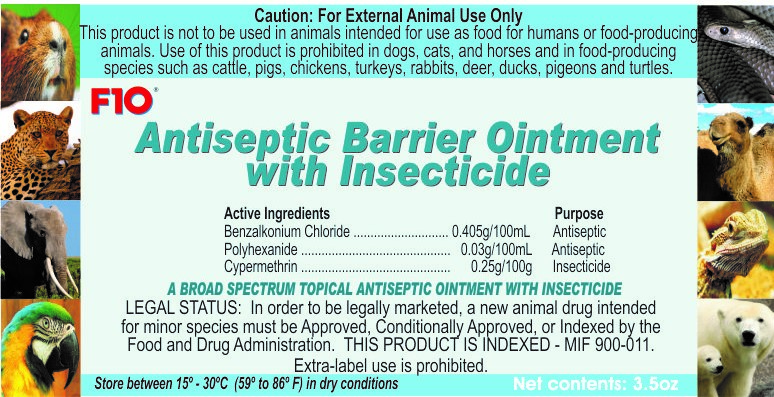 DRUG LABEL: F10
NDC: 86152-0111 | Form: OINTMENT
Manufacturer: Health and Hygiene (Pty) Ltd
Category: animal | Type: OTC ANIMAL DRUG LABEL
Date: 20220126

ACTIVE INGREDIENTS: BENZALKONIUM CHLORIDE 0.4 g/100 g; BIGUANIDE 0.03 g/100 g; CYPERMETHRIN 0.25 g/100 g

F10 Antiseptic Barrier Ointment with Insecticide

Human Warnings

Not for use in Humans. Keep out of reach of children

Uses

For use as a topical antiseptic for surface wounds, to repel flies and to treat infestations due to fly strike.

Directions for use

Clean the wound prior to application. Apply a layer of ointment over the entire wound site. Repeat once a week, if necessary or as advised by a veterinarian. This product is water soluble and should be reapplied if animals bathed or exposed to rain.

Packaging Label

Front Panel

US224-10 20 Antiseptic Barrier ointment with Insecticide 100g FP.jpg

Packaging Label

Back Panel

US224-10 20 Antiseptic Barrier ointment with Insecticide 100g BP.jpg